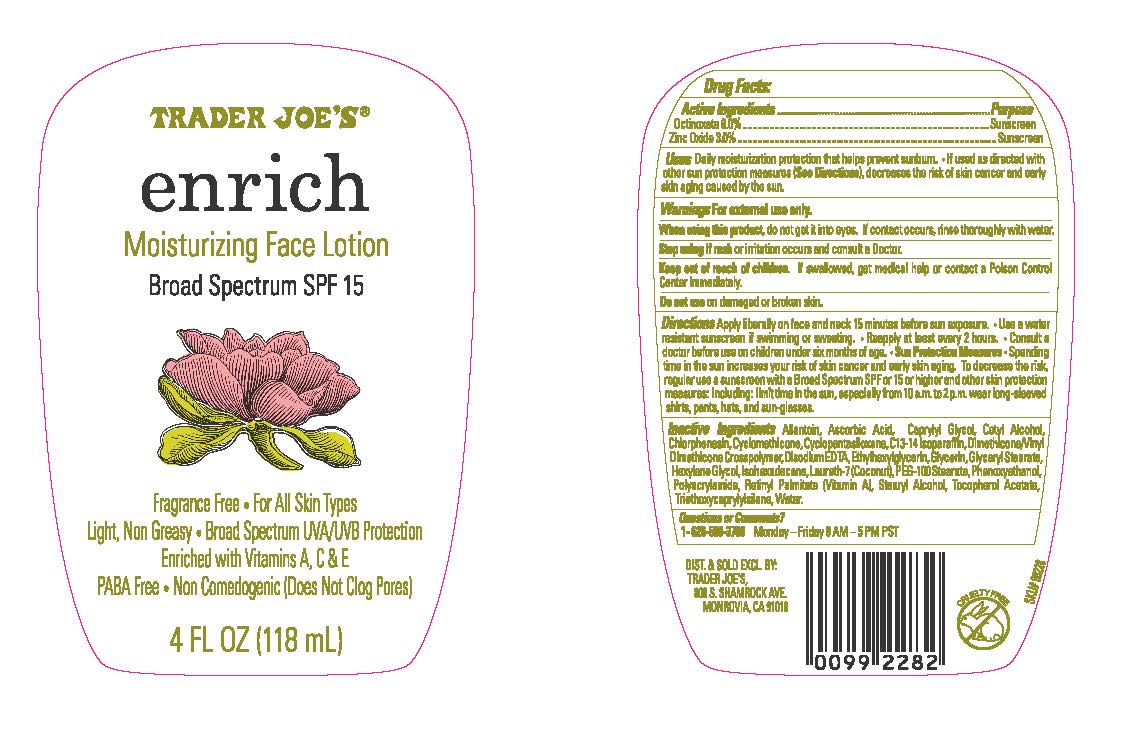 DRUG LABEL: TRADER JOES ENRICH MOISTURIZING FACE
NDC: 71270-252 | Form: LOTION
Manufacturer: Trader Joe's Company
Category: otc | Type: HUMAN OTC DRUG LABEL
Date: 20241022

ACTIVE INGREDIENTS: OCTINOXATE 6 g/100 mL; ZINC OXIDE 3 g/100 mL
INACTIVE INGREDIENTS: ALLANTOIN; ASCORBIC ACID; CAPRYLYL GLYCOL; CETYL ALCOHOL; CHLORPHENESIN; CYCLOMETHICONE; CYCLOMETHICONE 5; C13-14 ISOPARAFFIN; DIMETHICONE/VINYL DIMETHICONE CROSSPOLYMER (SOFT PARTICLE); EDETATE DISODIUM; ETHYLHEXYLGLYCERIN; GLYCERIN; GLYCERYL MONOSTEARATE; HEXYLENE GLYCOL; ISOHEXADECANE; LAURETH-7; PEG-100 STEARATE; PHENOXYETHANOL; POLYACRYLAMIDE (10000 MW); VITAMIN A PALMITATE; STEARYL ALCOHOL; .ALPHA.-TOCOPHEROL ACETATE; TRIETHOXYCAPRYLYLSILANE

TRADER JOE’S (as PLD) - ENRICH MOISTURIZING FACE LOTION - BROAD SPECTRUM SPF 15 (71270-252)

Active ingredient

Octinoxate 6%

Zinc Oxide 3%

Purpose

Sunscreen

Uses

- Daily moisturizer that helps prevent sunburn.
- If used as directed with other sun protection measures (See Directions), decreases the risk of skin cancer and early skin aging caused by the sun.

Warnings

For external use only.

When using this product, do not get into eyes. If contact occurs, rinse thoroughly with water.

Stop using if rashor irritation occurs and consult a Doctor.

Do not useon damaged or broken skin.

Keep out of reach of children.If swallowed, get medical help or contact a Poison Control Center immediately.

Directions

- Apply liberally on face and neck 15 minutes before sun exposure.
- Use a water resistant sunscreen if swimming or sweating.
- Reapply at least every 2 hours.
- Consult a doctor before use on children under six months of age.

Sun Protection Measures.Spending time in the sun increases your risk of skin cancer and early skin aging. To decrease this risk, regularly use a sunscreen with a Broad Spectrum SPF 15 value or higher along with other sun protection measures including: limit time in the sun, especially from 10 a.m. – 2 p.m., wear long sleeved shirts, pants, hats and sunglasses.

Inactive ingredients

ALLANTOIN, ASCORBIC ACID, CAPRYLYL GLYCOL, CETYL ALCOHOL, CHLORPHENESIN, CYCLOMETHICONE, CYCLOPENTASILOXANE, C13-14 ISOPARAFFIN, DIMETHICONE/VINYL DIMETHICONE CROSS POLYMER, DISODIUM EDTA, ETHYLHEXYLGLYCERIN, GLYCERIN, GLYCERYL STEARATE, HEXYLENE GLYCOL, ISOHEXADECANE, LAURETH-7 (COCONUT), PEG-100 STEARATE, PHENOXYETHANOL, POLYACRYLAMIDE, RETINYL PALMITATE (VITAMIN A), STEARYL ALCOHOL, TOCOPHERYL ACETATE, TRIETHOXYCAPRYLYLSILANE, WATER.

Questions or comments?

1- 626-599-3700Monday – Friday 9 AM – 5 PM PST